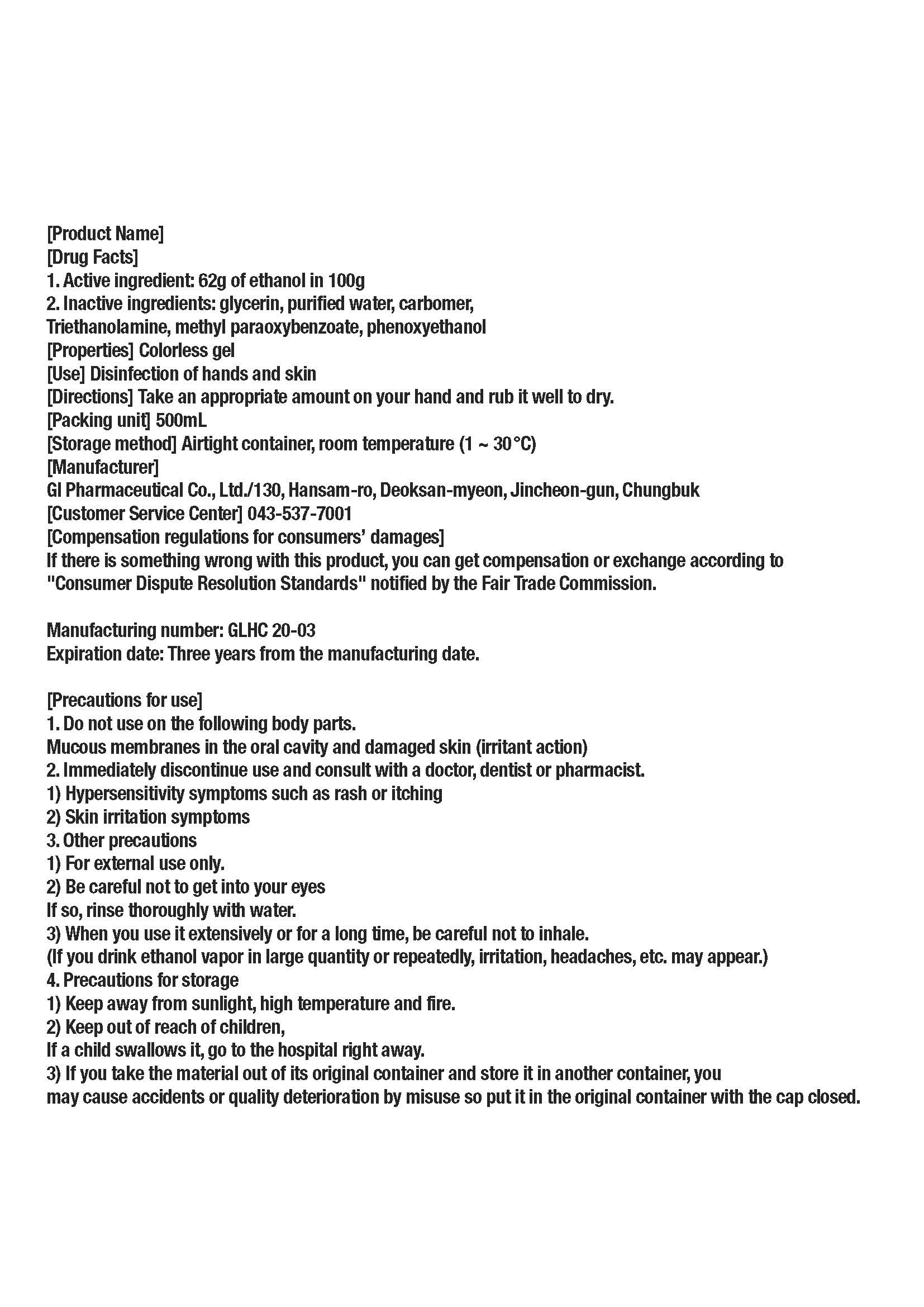 DRUG LABEL: The Blue gel
NDC: 74713-0002 | Form: GEL
Manufacturer: GL Pharm Co Ltd
Category: otc | Type: HUMAN OTC DRUG LABEL
Date: 20200410

ACTIVE INGREDIENTS: ALCOHOL 62 g/100 mL
INACTIVE INGREDIENTS: WATER; GLYCERIN; METHYLPARABEN; ACRYLIC ACID; TROLAMINE; PHENOXYETHANOL

Drug Facts

ACTIVE INGREDIENT

alcohol 64%

INACTIVE INGREDIENT

Glycerin
Carbopol
Triethanolamine
Methyl paraben
Phenoxy ethanol
Pure water

PURPOSE

Disinfection of hands and skin

KEEP OUT OF REACH OF THE CHILDREN

INDICATIONS AND USAGE

Take an appropriate amount on your hand and rub it well to dry.

WARNINGS

■ Flammable. Keep away from fire or flame.

■ For external use only.

■ Do not use in eyes.

■ lf swallowed, get medical help promptly.

■ Stop use, ask doctor lf irritation occurs.

■ Keep out of reach of children.

DOSAGE AND ADMINISTRATION

for external use only